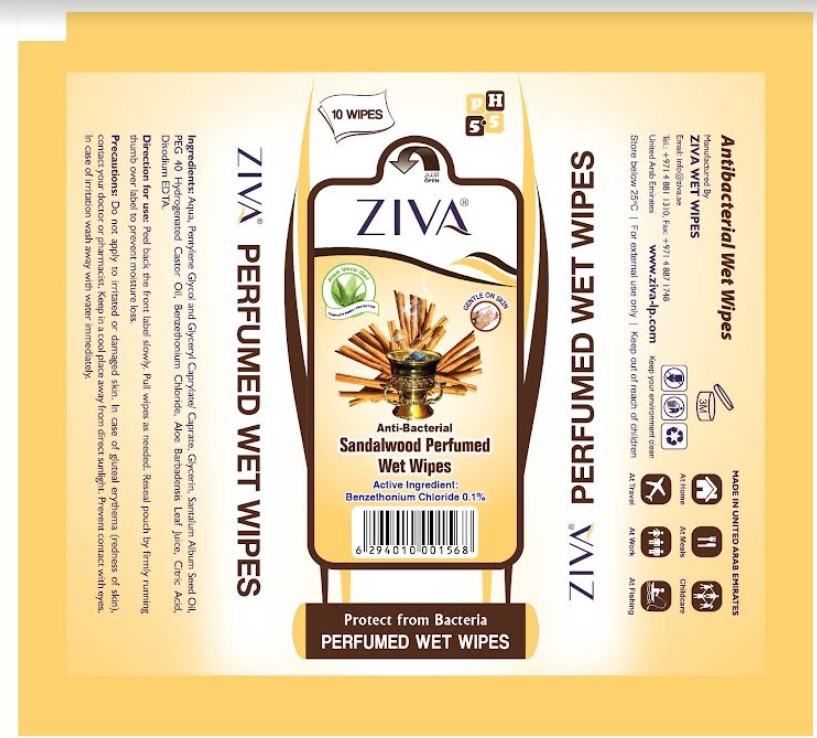 DRUG LABEL: ZIVA PERFUMED WIPES BAKHOOR
NDC: 81450-003 | Form: CLOTH
Manufacturer: Ziva Wetwipes FZCo
Category: otc | Type: HUMAN OTC DRUG LABEL
Date: 20211223

ACTIVE INGREDIENTS: BENZETHONIUM CHLORIDE 0.1 g/100 mL
INACTIVE INGREDIENTS: GLYCERIN; GLYCERYL CAPRYLATE/CAPRATE; HYDROGENATED CASTOR OIL; CITRIC ACID MONOHYDRATE; EDETATE DISODIUM; PENTYLENE GLYCOL; WATER; ALOE VERA LEAF; SANTALUM ALBUM SEED OIL

Drug Facts

Active Ingredient:

Benzethonium Chloride 0.1%

Direction for use:

Peel back the front label slowly. Pull wipes as needed. Reseal pouch by firmly running thumb over label to prevent moisture loss.

Precautions:

For external use only. Do not apply to irritated or damaged skin. In case of gluteal erythema (redness of skin), contact your doctor or pharmacist. Keep in a cool place away from direct sun light. Prevent contact with eyes. In case of irritation wash away with water immediately.

Store below 25°C | For external use only | Keep out of reach of children

Ingredients:

Aqua, Pentylene Glycol and Glyceryl Caprylate / Caprate, Perfume, PEG 40 Hydrogenated Castor Oil, Aloe Barbadensis Leaf Juice, Citric Acid, Disodium EDTA.